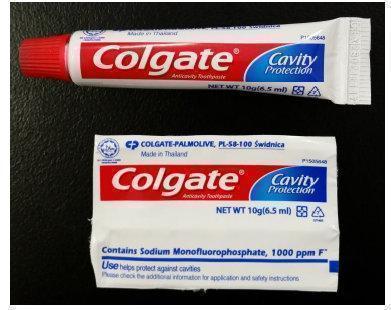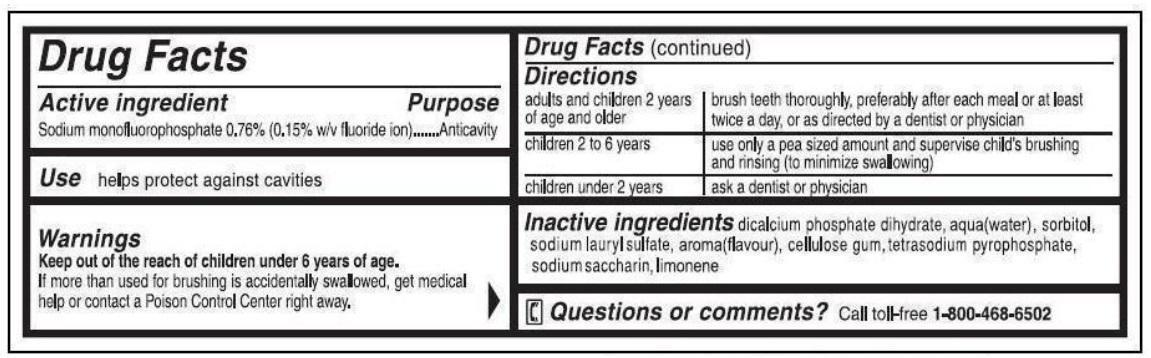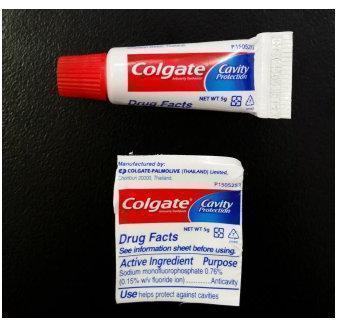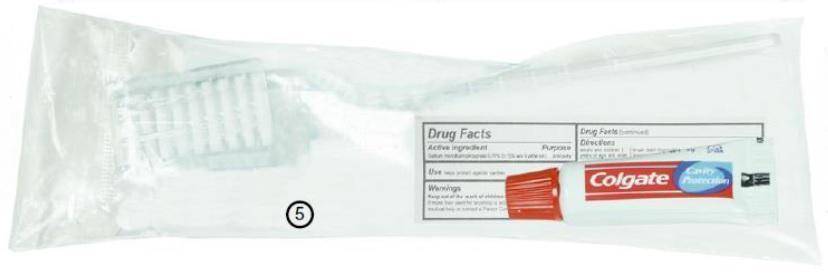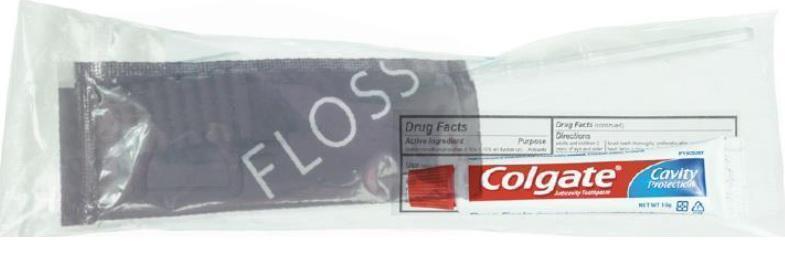 DRUG LABEL: Colgate
NDC: 69491-060 | Form: PASTE
Manufacturer: Buzz Export Services Pty., Ltd.
Category: otc | Type: HUMAN OTC DRUG LABEL
Date: 20211227

ACTIVE INGREDIENTS: SODIUM FLUORIDE 1.5 mg/1 g
INACTIVE INGREDIENTS: CALCIUM PHOSPHATE, DIBASIC, DIHYDRATE; WATER; SORBITOL; SODIUM LAURYL SULFATE; SODIUM PYROPHOSPHATE; SACCHARIN SODIUM

DENTAL KITS - COLGATE TOOTHPASTE

Active Ingredient

Sodium monofluorophosphate 0.76% (0.15% w/v fluoride ion)

Purpose

Anticavity

Use

helps protect against cavities

Keep out of reach of children under 6 years of age.

If more than used for brushing is accidentally swallowed, get medical help or contact a Poison Control Center right away.

Directions

adults and children 2 years of age and older: brush teeth thoroughly, preferably after each meal or at least twice a day, or as directed by a dentist or physician

children 2 to 6 years: use only a pea sized amount and supervise child's brushing and rinsing (to minimize swallowing)

children under 2 years: ask a dentist or physician

Inactive Ingredients

dicalcium phosphate dihydrate, water, glycerin, sodium lauryl sulfate, cellulose gum, flavor, tetrasodium pyrophosphate, sodium saccharin

Questions?

1-800-468-6502

Dist. by: COLGATE-PALMOLIVE COMPANY New York, NY 10022

DENTAL KIT - COLGATE TOOTHPASTE 5g Labels

TUBE LABELING:

KIT PACKAGING:

DENTAL KIT - COLGATE TOOTHPASTE 10g

TUBE LABELING:

KIT PACKAGING: